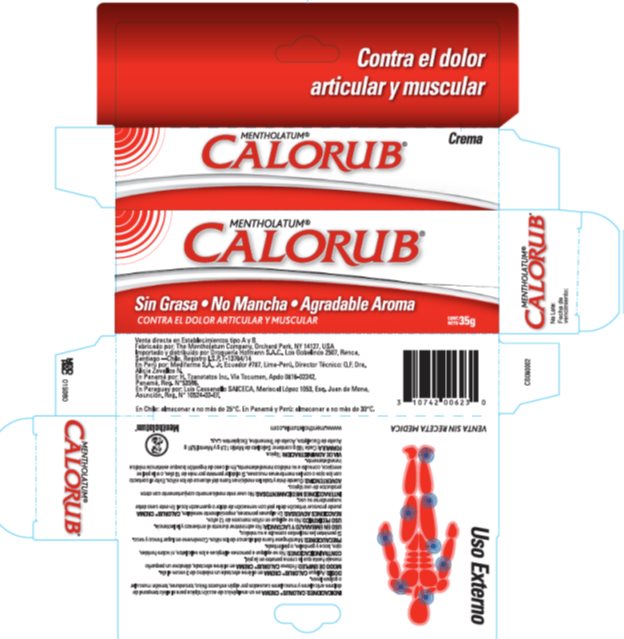 DRUG LABEL: Calorub
NDC: 10742-2120 | Form: CREAM
Manufacturer: The Mentholatum Company
Category: otc | Type: HUMAN OTC DRUG LABEL
Date: 20180702

ACTIVE INGREDIENTS: MENTHOL, UNSPECIFIED FORM 59.1 mg/1 g; METHYL SALICYLATE 128 mg/1 g
INACTIVE INGREDIENTS: CETOSTEARYL ALCOHOL; EUCALYPTUS OIL; LANOLIN; LIGHT MINERAL OIL; PROPYLENE GLYCOL; WATER; QUATERNIUM-15; SODIUM CETOSTEARYL SULFATE; TURPENTINE OIL

Drug Facts